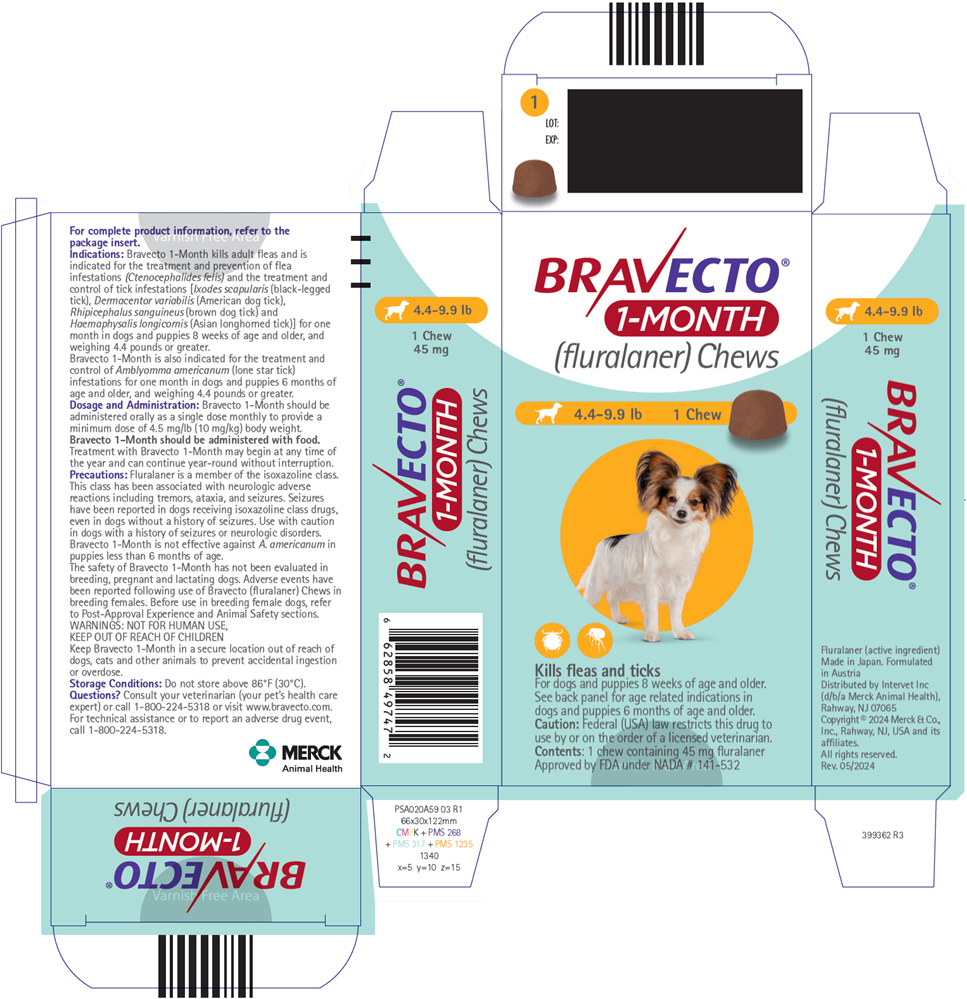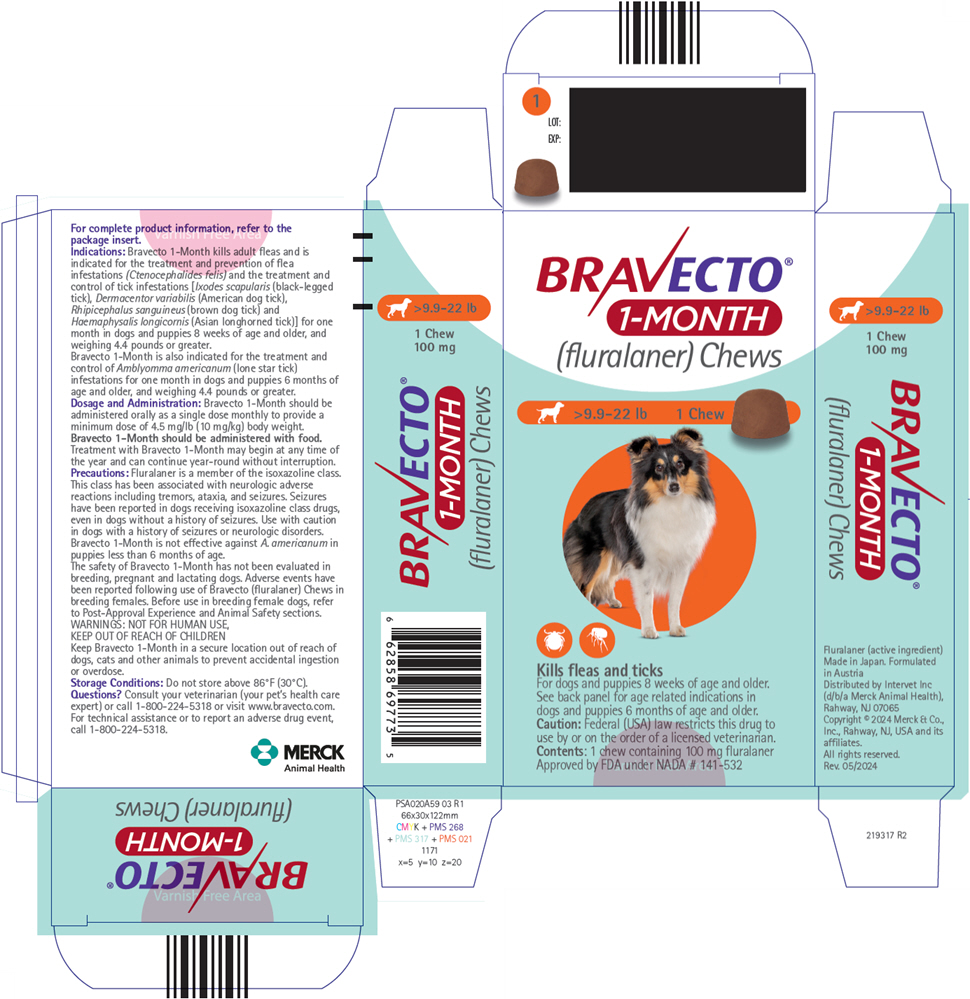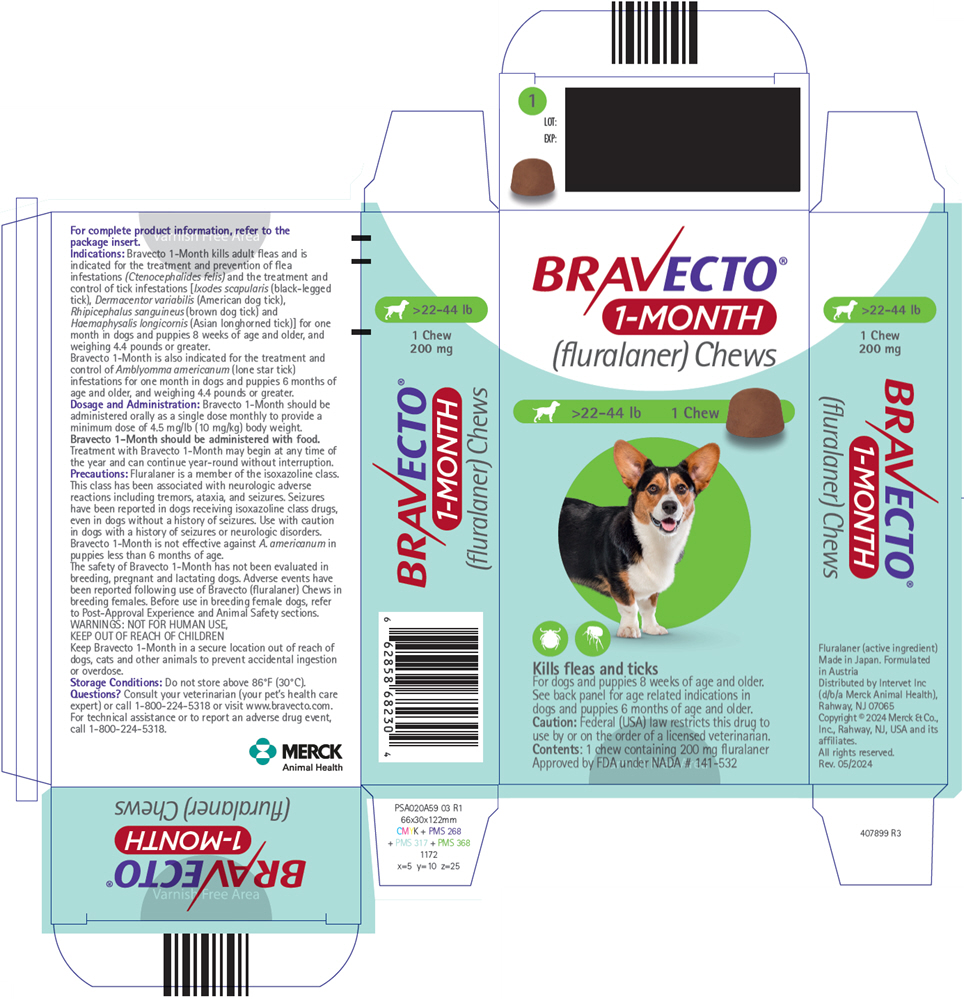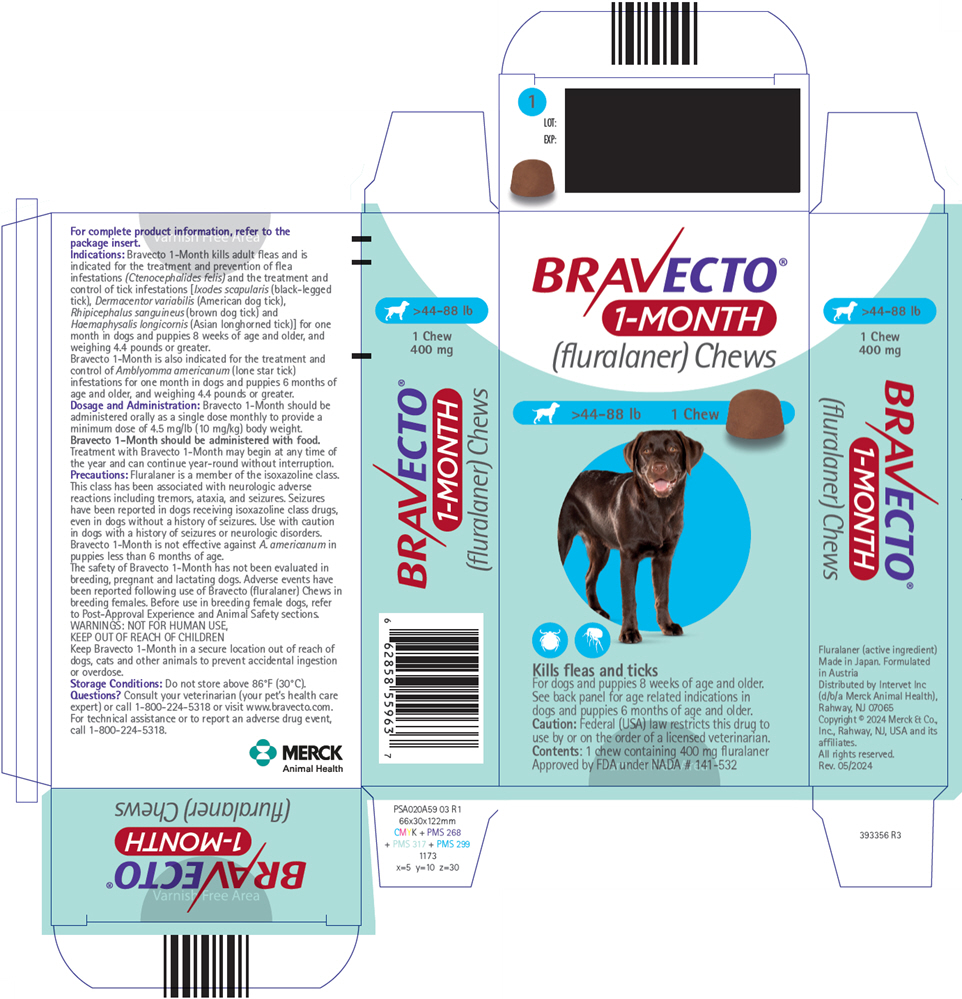 DRUG LABEL: Bravecto 1-Month
NDC: 0061-4368 | Form: TABLET, CHEWABLE
Manufacturer: Merck Sharp & Dohme Corp.
Category: animal | Type: PRESCRIPTION ANIMAL DRUG LABEL
Date: 20251126

ACTIVE INGREDIENTS: FLURALANER 45 mg/1 1

BRAVECTO®
1-MONTH
(fluralaner) Chews for Dogs

Caution:

Federal (USA) law restricts this drug to use by or on the order of a licensed veterinarian.

Description:

Bravecto 1-Month (fluralaner) is a flavored chew formulated to provide a minimum dose of 4.5 mg/lb (10 mg/kg) body weight of fluralaner.

The chemical name of fluralaner is (±)-4-[5-(3,5-dichlorophenyl)-5-(trifluoromethyl)-4,5-dihydroisoxazol-3-yl]-2-methyl-N-[2-oxo-2-(2,2,2-trifluoroethylamino)ethyl]benzamide.

Indications:

Bravecto 1-Month kills adult fleas and is indicated for the treatment and prevention of flea infestations (Ctenocephalides felis) and the treatment and control of tick infestations [Ixodes scapularis (black-legged tick), Dermacentor variabilis (American dog tick), Rhipicephalus sanguineus (brown dog tick) and Haemaphysalis longicornis (Asian longhorned tick)] for one month in dogs and puppies 8 weeks of age and older, and weighing 4.4 pounds or greater.

Bravecto 1-Month is also indicated for the treatment and control of Amblyomma americanum (lone star tick) infestations for one month in dogs and puppies 6 months of age and older, and weighing 4.4 pounds or greater.

Dosage and Administration:

Bravecto 1-Month should be administered orally as a single dose monthly according to the Dosage Schedule below to provide a minimum dose of 4.5 mg/lb (10 mg/kg) fluralaner.

Bravecto 1-Month should be administered with food.

Dosage Schedule
Body Weight Ranges (lb) | Fluralaner content (mg) | Chews Administered
4.4 – 9.9 | 45 | One
>9.9 – 22.0 | 100 | One
>22.0 – 44.0 | 200 | One
>44.0 – 88.0 | 400 | One
>88.0 – 123.0 [Dogs over 123.0 lb should be administered the appropriate combination of chews] | 560 | One

Treatment with Bravecto 1-Month may begin at any time of the year and can continue year-round without interruption.

Contraindications:

There are no known contraindications for the use of the product.

Warnings:

Not for human use. Keep this and all drugs out of the reach of children. Keep the product in the original packaging until use, in order to prevent children from getting direct access to the product. Do not eat, drink or smoke while handling the product. Wash hands thoroughly with soap and water immediately after use of the product.

Keep Bravecto 1-Month in a secure location out of reach of dogs, cats, and other animals to prevent accidental ingestion or overdose.

Precautions:

Fluralaner is a member of the isoxazoline class. This class has been associated with neurologic adverse reactions including tremors, ataxia, and seizures. Seizures have been reported in dogs receiving isoxazoline class drugs, even in dogs without a history of seizures. Use with caution in dogs with a history of seizures or neurologic disorders.

Bravecto 1-Month is not effective against A. americanum in puppies less than 6 months of age (see Effectiveness).

The safety of Bravecto 1-Month has not been evaluated in breeding, pregnant and lactating dogs (see Animal Safety).

Adverse Reactions:

In a well-controlled U.S. field study, which included 271 dogs (201 dogs were administered Bravecto 1-Month every 30 days and 70 dogs were administered an oral active control [an isoxazoline] every 30 days), there were no serious adverse reactions associated with treatment. Over the 90-day study period, all observations of potential adverse reactions were recorded.

Dogs with Adverse Reactions in the Field Study
Adverse Reaction (AR) | Fluralaner Group: Percentage of Dogs with the AR during the 90-Day Study (n= 201 dogs) | Active Control Group: Percentage of Dogs with the AR during the 90-Day Study (n= 70 dogs)
Pruritus | 7.0% | 10.0%
Diarrhea | 3.0% | 4.3%
Vomiting | 3.0% | 4.3%
Decreased Appetite | 3.0% | 0.0%
Liver enzymes (serum ALT or ALP) greater than twice the upper reference range [Alanine aminotransferase (ALT); alkaline phosphatase (ALP)] | 1.0% | 1.4%
Lethargy | 1.0% | 1.4%
Weight loss (>15%) | 0.5% | 0.0%

One dog in the Bravecto 1-Month group with a history of seizures managed with anticonvulsant medication had seizure activity 28 days after its first dose; the dog received its second dose later the same day. No additional seizures occurred during the study. One dog in the control group with no history of seizures had seizure activity 12 days after its second dose. The dog was started on anticonvulsant medication and no additional seizures occurred during the study.

During the palatability assessment, four dogs coughed within 1 hour of dosing with Bravecto 1-Month. Palatability was not assessed in the control group.

In well-controlled laboratory effectiveness studies, one dog and three puppies administered Bravecto 1-Month had diarrhea (with or without blood).

Post-Approval Experience (2024):

The following adverse events are based on post-approval adverse drug experience reporting for Bravecto 1-Month. Not all adverse events are reported to FDA/CVM. It is not always possible to reliably estimate the adverse event frequency or establish a causal relationship to product exposure using these data.

The following adverse events reported for dogs are listed in decreasing order of reporting frequency:

Vomiting, lethargy, diarrhea, anorexia, tremors, ataxia, seizure, pruritus, and allergic reactions (including hives, swelling, and erythema).

The following reproductive adverse events have been reported following use of Bravecto (fluralaner) Chews: birth defects (including limb deformities and cleft palate), stillbirth, and abortion.

To report suspected adverse events, for technical assistance or to obtain a copy of the Safety Data Sheet (SDS), contact Merck Animal Health at 1-800-224-5318. Additional information can be found at www.bravecto.com. For additional information about adverse drug experience reporting for animal drugs, contact FDA at 1-888-FDA-VETS or online at http://www.FDA.gov/reportanimalae.

Clinical Pharmacology:

Peak fluralaner concentrations are achieved between 1 and 3 days following single or multiple oral administrations of Bravecto 1-Month to young puppies and adult dogs. The elimination half-life ranges from 5.0 to 8.5 days for puppies and 12.6 to 15.7 days for adult dogs. Due to reduced drug bioavailability in the fasted state, Bravecto 1-Month should be administered with food.

Mode of Action:

Fluralaner is for systemic use and belongs to the class of isoxazoline-substituted benzamide derivatives. Fluralaner is an inhibitor of the arthropod nervous system. The mode of action of fluralaner is the antagonism of the ligand-gated chloride channels (gamma-aminobutyric acid (GABA)-receptor and glutamate-receptor).

Effectiveness:

Treatment and Prevention of Flea Infestations:

In well-controlled laboratory studies in dogs 6 months of age and older, Bravecto 1-Month started killing fleas within 4 hours after treatment and was > 99% effective by 12 hours after treatment or post-infestation for 35 days.

In a well-controlled laboratory study in dogs 8 weeks of age and older, Bravecto 1-Month demonstrated 100% effectiveness against fleas for 30 days.

In a well-controlled 90-day U.S. field study conducted in households with existing flea infestations, the effectiveness of Bravecto 1-Month against fleas on Day 30, 60, and 90 visits compared with baseline was 99.6%, 99.9%, and 99.9%, respectively. Dogs with signs of flea allergy dermatitis showed improvement in erythema, alopecia, papules, scales, crusts, and excoriation as a direct result of eliminating flea infestations.

Treatment and Control of Tick Infestations:

In well-controlled laboratory studies in dogs 8 weeks of age and older, Bravecto 1-Month demonstrated ≥97.7% effectiveness against Rhipicephalus sanguineus and Haemaphysalis longicornis ticks at 48 hours after treatment or infestation for 30 days.

In well-controlled laboratory studies, fluralaner, the active ingredient in Bravecto 1-Month, demonstrated effectiveness against Ixodes scapularis and Dermacentor variabilis.

In well-controlled laboratory studies in dogs 6 months of age and older, Bravecto 1-Month demonstrated >96% effectiveness against Amblyomma americanum at 48- and 72-hours after treatment or infestation for 31 days.

Bravecto 1-Month failed to demonstrate >90% effectiveness against Amblyomma americanum in 8-week-old puppies.

Palatability:

In a well-controlled U.S. field study, which included 579 doses administered to 201 dogs, 81.5% of dogs voluntarily consumed Bravecto 1-Month within 5 minutes, an additional 9.0% voluntarily consumed Bravecto 1-Month within 5 minutes when offered with food, and 9.5% required forced administration.

Animal Safety:

Margin of Safety Study:

In a margin of safety study, Bravecto 1-Month was administered orally to 8-week old puppies at 1, 3, and 5× the maximum labeled dose of 22.5 mg/kg with 8 dogs per group at three, 30-day intervals (Days 1, 31 and 61). The dogs in the control group were untreated.

There were no clinically-relevant, treatment-related effects on body weights, food consumption, organ weights, hematology, C-reactive protein, coagulation profile, urinalysis, gross pathology and histopathology. Diarrhea and mucoid or discolored feces were the most common observations, occurring at a similar incidence in the treated and control groups. Vomiting was noted in one dog in the 5× group and one dog in the control group on Day 2. Splayed hind limbs were noted in one dog in the 1× treatment group post-dose on Day 61. Tremors were noted in one dog in each of the 3 fluralaner dose groups on Day 1 at 4 hours post-dose. Trembling was noted in one dog in the 1× group on Day 2. Blood urea nitrogen (BUN) was elevated in one dog in the 3× group on Day 8. BUN and serum creatinine were elevated in one dog in the 5× group on Day 85.

Reproductive Safety Study:

Reproductive safety was evaluated for fluralaner, the active ingredient in BRAVECTO 1-Month (fluralaner). Fluralaner was administered orally to intact, reproductively-sound male and female Beagles at a dose of up to 168 mg/kg on three to four occasions at 8-week intervals. The dogs in the control group were untreated. There were no clinically-relevant, treatment-related effects on the body weights, food consumption, reproductive performance, semen analysis, litter data, gross necropsy (adult dogs) or histopathology findings (adult dogs and puppies). One adult dog in the treated group suffered a seizure during the course of the study (46 days after the third treatment). Abnormal salivation was observed on 17 occasions: in six treated dogs (11 occasions) after dosing and four control dogs (6 occasions).

The following abnormalities were noted in 7 pups from 2 of the 10 dams in only the treated group during gross necropsy examination: limb deformity (4 pups), enlarged heart (2 pups), enlarged spleen (3 pups), and cleft palate (2 pups). During veterinary examination at Week 7, two pups from the control group had inguinal testicles, and two and four pups from the treated group had inguinal and cryptorchid testicles, respectively. No undescended testicles were observed at the time of necropsy (days 50 to 71).

In a well-controlled field study Bravecto 1-Month was used concurrently with other medications, such as vaccines, anthelmintics, antibiotics (including topicals), steroids, analgesics, and anesthetics. No adverse reactions were observed from the concurrent use of Bravecto 1-Month with other medications.

Storage Conditions:

Do not store above 86°F (30°C).

How Supplied:

Bravecto 1-Month is available in five strengths (45, 100, 200, 400, and 560 mg fluralaner per chew). Each chew is packaged individually into aluminum foil blister packs sealed with a peelable paper backed foil lid stock. Product may be packaged in 1, 3, or 4 chews per package.

Approved by FDA under NADA # 141-532

Distributed by:
Intervet Inc (d/b/a Merck Animal Health), Rahway, NJ 07065
Formulated in Austria

Copyright © 2024 Merck & Co., Inc., Rahway, NJ, USA and its affiliates.
All rights reserved

Rev: 05/2024

399706 R3

PRINCIPAL DISPLAY PANEL - 45 mg Chew Blister Pack Carton

BRAVECTO®
1-MONTH
(fluralaner) Chews

4.4-9.9 lb
1 Chew

Kills fleas and ticks

For dogs and puppies 8 weeks of age and older.
See back panel for age related indications in
dogs and puppies 6 months of age and older.

Caution: Federal (USA) law restricts this drug to
use by or on the order of a licensed veterinarian.
Contents: 1 chew containing 45 mg fluralaner
Approved by FDA under NADA # 141-532

PRINCIPAL DISPLAY PANEL - 100 mg Chew Blister Pack Carton

BRAVECTO®
1-MONTH
(fluralaner) Chews

>9.9-22 lb
1 Chew

Kills fleas and ticks

For dogs and puppies 8 weeks of age and older.
See back panel for age related indications in
dogs and puppies 6 months of age and older.

Caution: Federal (USA) law restricts this drug to
use by or on the order of a licensed veterinarian.
Contents: 1 chew containing 100 mg fluralaner
Approved by FDA under NADA # 141-532

PRINCIPAL DISPLAY PANEL - 200 mg Chew Blister Pack Carton

BRAVECTO®
1-MONTH
(fluralaner) Chews

>22-44 lb
1 Chew

Kills fleas and ticks

For dogs and puppies 8 weeks of age and older.
See back panel for age related indications in
dogs and puppies 6 months of age and older.

Caution: Federal (USA) law restricts this drug to
use by or on the order of a licensed veterinarian.
Contents: 1 chew containing 200 mg fluralaner
Approved by FDA under NADA # 141-532

PRINCIPAL DISPLAY PANEL - 400 mg Chew Blister Pack Carton

BRAVECTO®
1-MONTH
(fluralaner) Chews

>44-88 lb
1 Chew

Kills fleas and ticks

For dogs and puppies 8 weeks of age and older.
See back panel for age related indications in
dogs and puppies 6 months of age and older.

Caution: Federal (USA) law restricts this drug to
use by or on the order of a licensed veterinarian.
Contents: 1 chew containing 400 mg fluralaner
Approved by FDA under NADA # 141-532